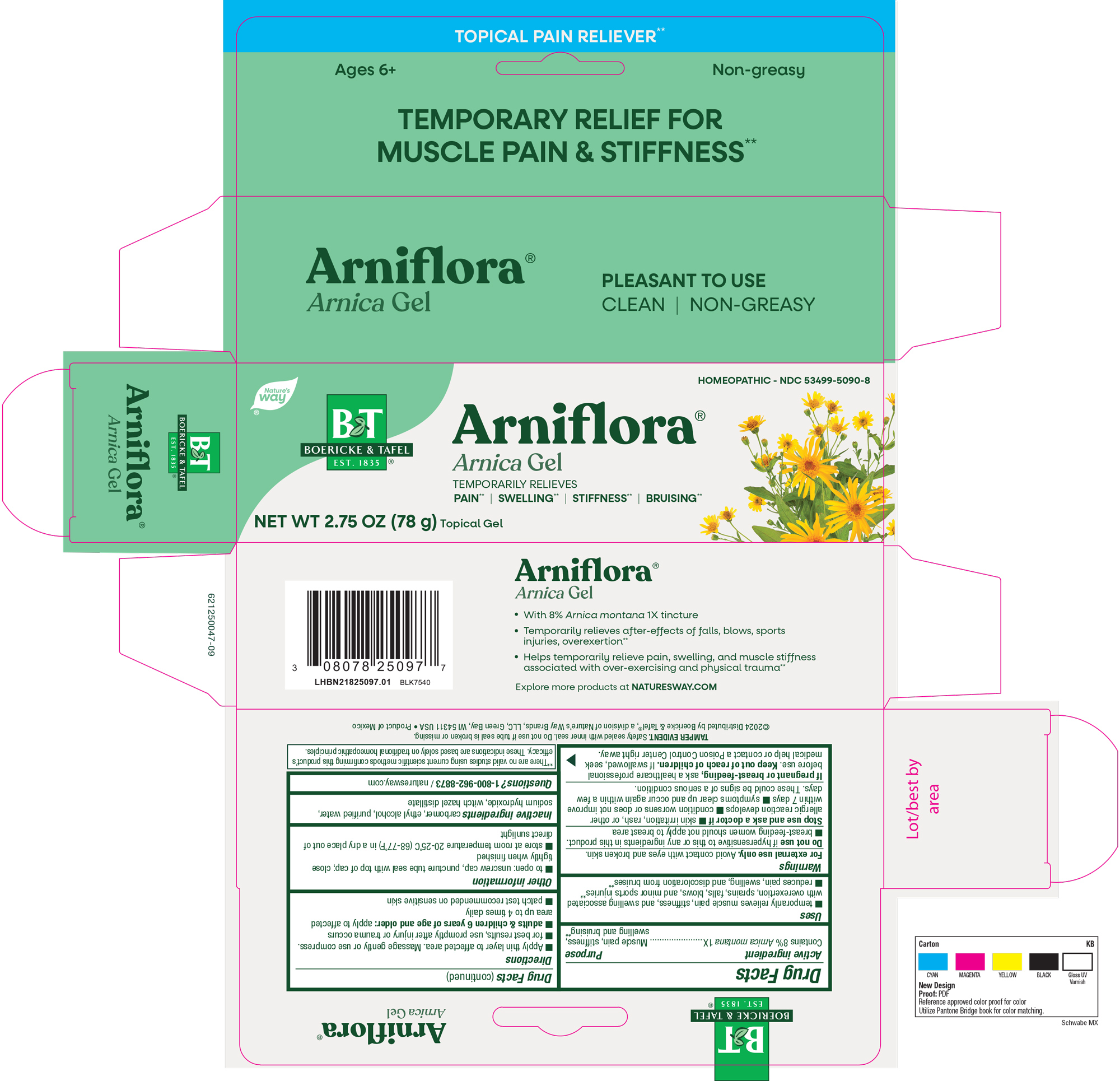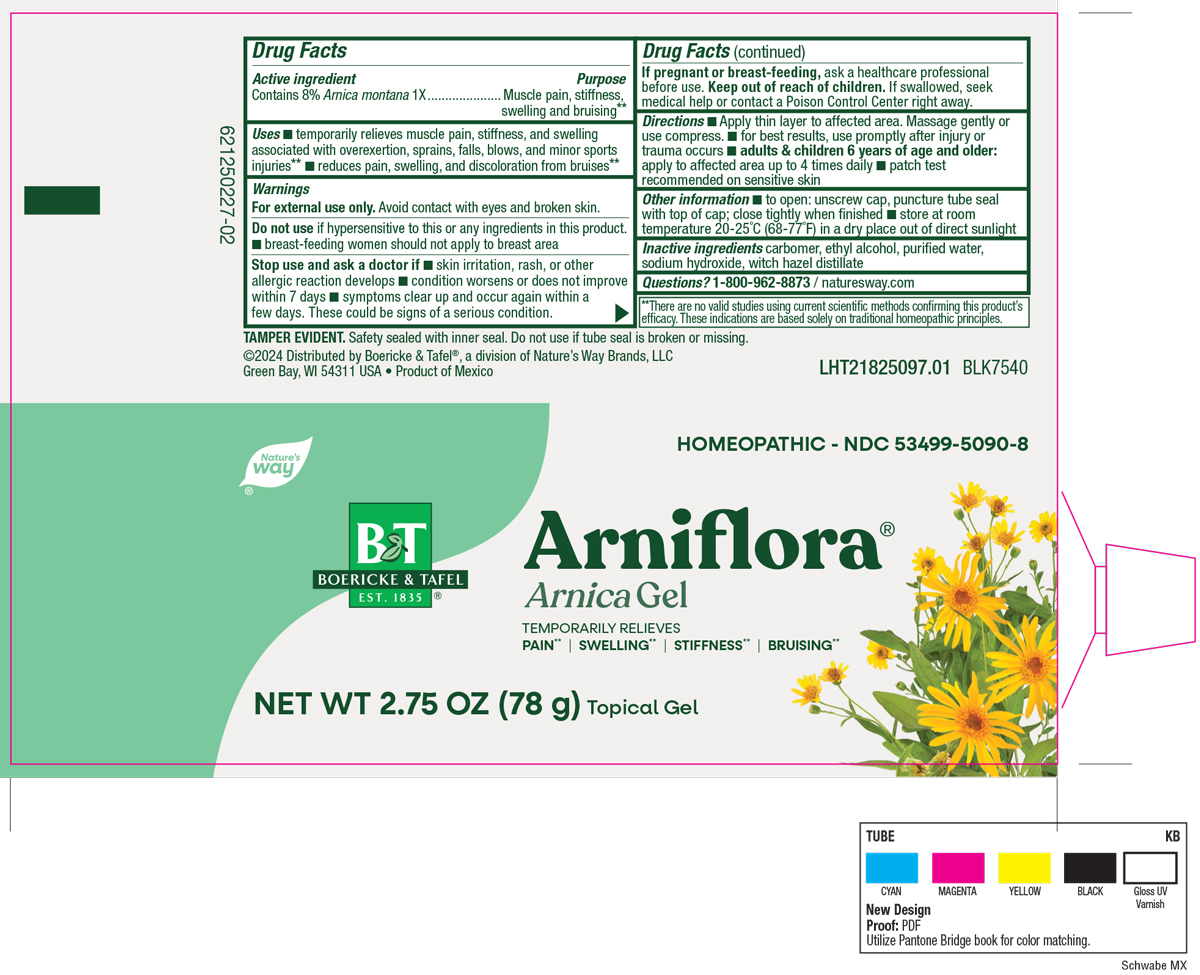 DRUG LABEL: Arniflora 
NDC: 53499-5090 | Form: GEL
Manufacturer: Schwabe North America, Inc
Category: homeopathic | Type: HUMAN OTC DRUG LABEL
Date: 20251121

ACTIVE INGREDIENTS: ARNICA MONTANA 1 [hp_X]/28 g
INACTIVE INGREDIENTS: ALCOHOL; CARBOMER HOMOPOLYMER TYPE C; WATER; WITCH HAZEL; SODIUM HYDROXIDE

Arniflora

Active Ingredient

Contains 8% Arnica montana 1X

Inactive Ingredients

Carbomer

Ethyl Alcohol

Purified Water

Sodium Hydroxide

Witch Hazel Distillate

Dosage and Administration

Directions

Apply thin layer to affected area. Massage gently or use compress.

For best results, use promptly after injury or trauma occurs.

Adults and children 6 years of age and older: apply to affected area up to 4 times daily.

Patch test recommended on sensitive skin.

Indications & Usage

Temporarily relieves muscle pain, stiffness, and swelling associated with overexertion, sprains, falls, blows, and minor sports injuries.

Reduces pain, swelling, and discoloration from bruises.

Purpose

Temporarily relieves muscle pain, stiffness, and swelling associated with overexertion, sprains, falls, blows, and minor sports injuries.

Reduces pain, swelling, and discoloration from bruises.

Warnings

For external use only.

Avoid contact with eyes and broken skin.

Do not use if hypersensitive to this or any ingredients in this product.

Breast-feeding women should not apply to breast area.

Stop Use

Stop use and ask a doctor if skin irritation, rash, or other allergic reaction develops, condition worsens or does not improve within 7 days, symptoms clear up and occur again within a few days.

These could be signs of a serious condition.

Pregnant or breast feeding

If pregnant or breast-feeding, ask a healthcare professional before use.

Keep out of reach of children

Overdose

If swallowed, seek medical help or contact a Poison Control Center right away.